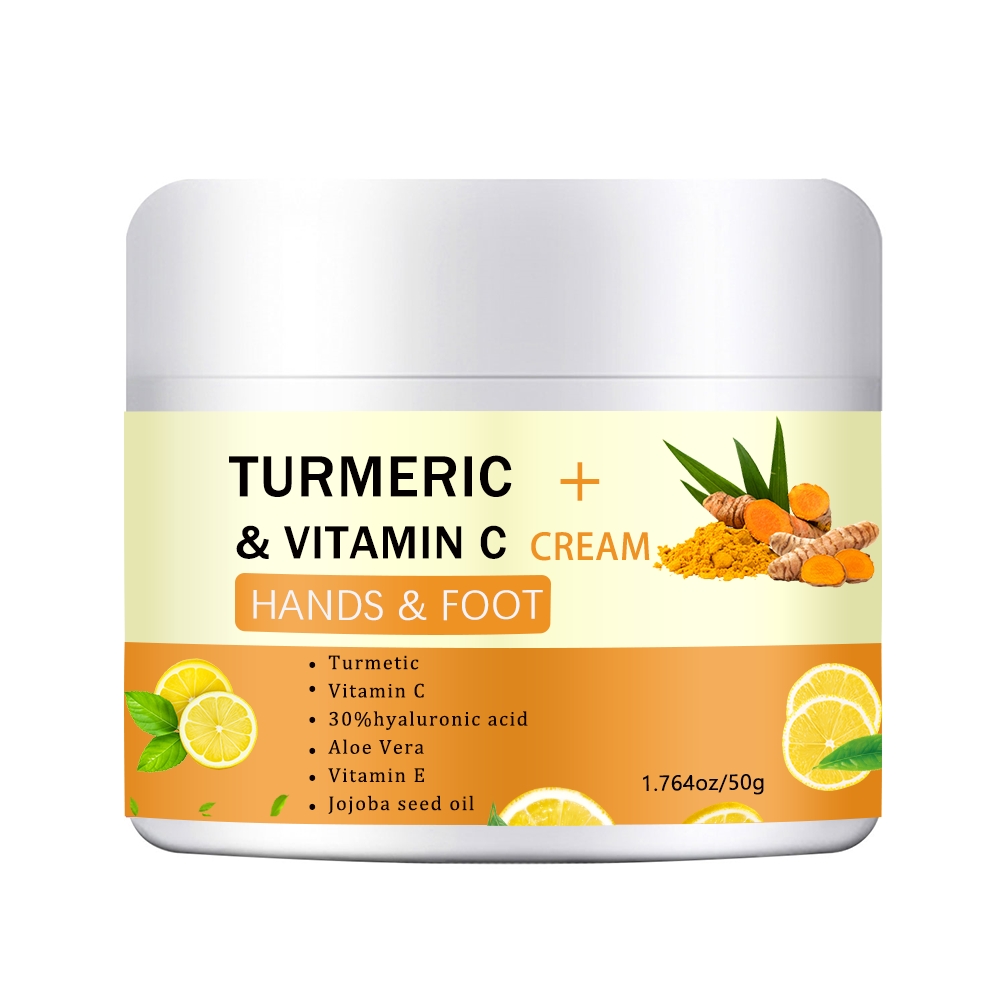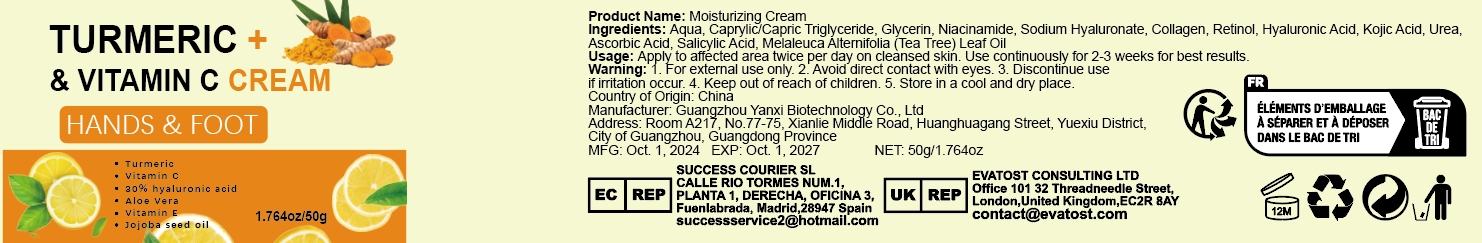 DRUG LABEL: Moisturizing Cream
NDC: 84025-269 | Form: CREAM
Manufacturer: Guangzhou Yanxi Biotechnology Co., Ltd
Category: otc | Type: HUMAN OTC DRUG LABEL
Date: 20241123

ACTIVE INGREDIENTS: NIACINAMIDE 2 mg/50 g; CAPRYLIC/CAPRIC TRIGLYCERIDE 3 mg/50 g
INACTIVE INGREDIENTS: WATER

DOSAGE AND ADMINISTRATION

Apply to affected area twice per day on cleansed skin.

WARNINGS

Keep out of children

INACTIVE INGREDIENT

Aqua

Keep out of children

INDICATIONS AND USAGE

For daily skin care

PURPOSE

Moisturizing skin